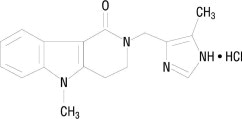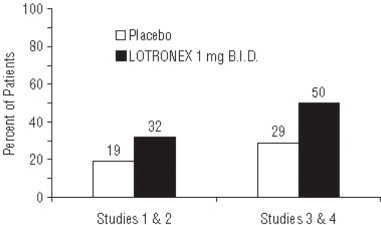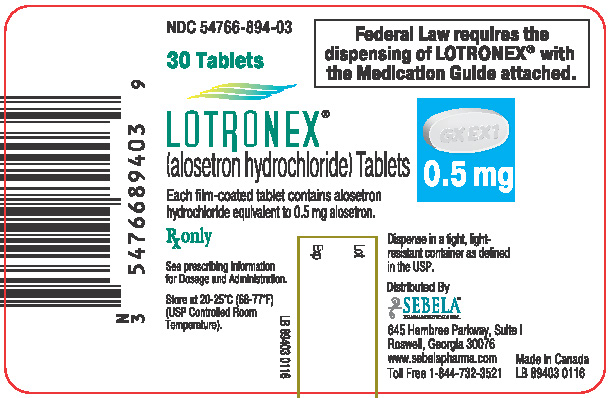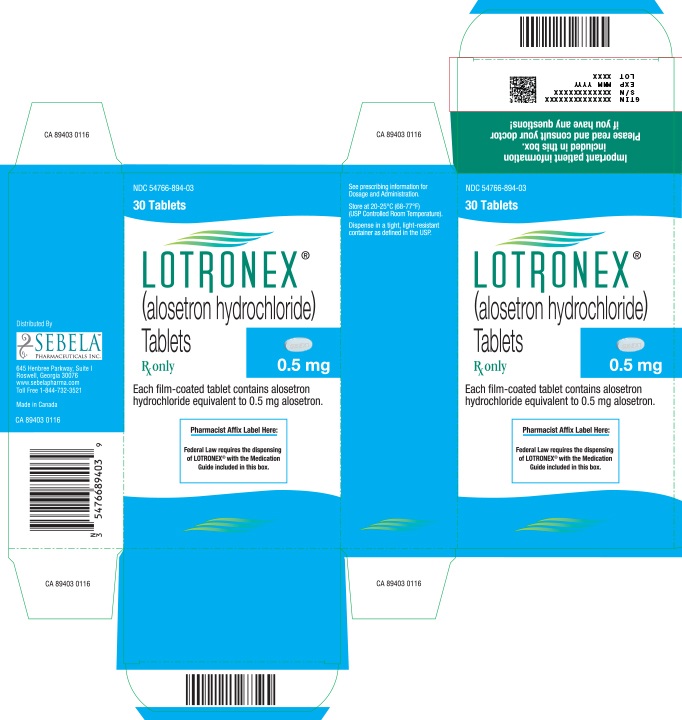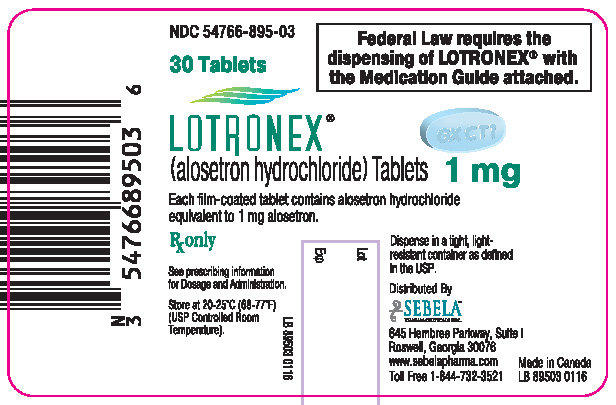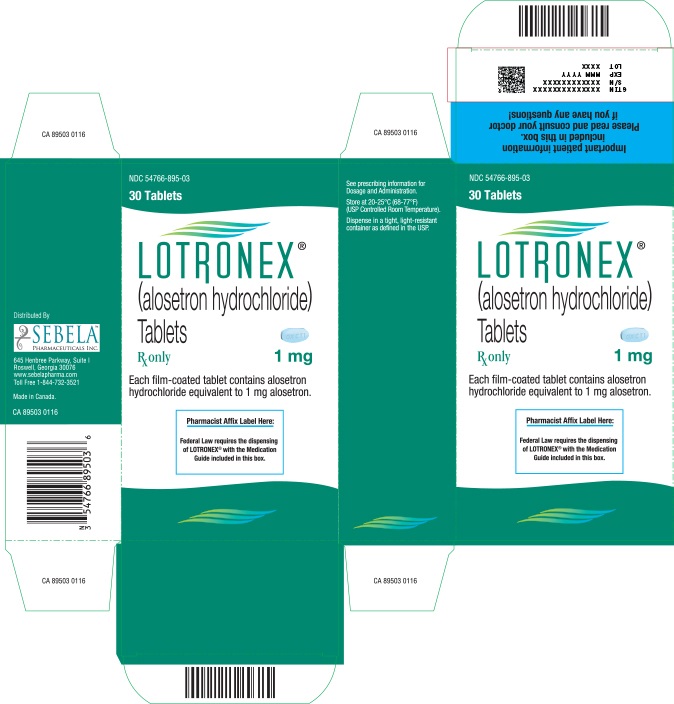 DRUG LABEL: LOTRONEX
NDC: 54766-894 | Form: TABLET
Manufacturer: Sebela Pharmaceuticals Inc.
Category: prescription | Type: HUMAN PRESCRIPTION DRUG LABEL
Date: 20251108

ACTIVE INGREDIENTS: ALOSETRON HYDROCHLORIDE 0.5 mg/1 1
INACTIVE INGREDIENTS: TRIACETIN; LACTOSE; MAGNESIUM STEARATE; CELLULOSE, MICROCRYSTALLINE; STARCH, CORN; HYPROMELLOSES; TITANIUM DIOXIDE

HIGHLIGHTS OF PRESCRIBING INFORMATION

These highlights do not include all the information needed to use LOTRONEX safely and effectively. See full prescribing information for LOTRONEX.
LOTRONEX (alosetron hydrochloride) Tablets
Initial U.S. Approval: 2000

WARNING: SERIOUS GASTROINTESTINAL ADVERSE REACTIONS

See full prescribing information for complete boxed warning.

Infrequent but serious gastrointestinal adverse reactions have been reported with the use of LOTRONEX. These events, including ischemic colitis and serious complications of constipation, have resulted in hospitalization and, rarely, blood transfusion, surgery, and death.

- LOTRONEX is indicated only for women with severe diarrhea-predominant irritable bowel syndrome (IBS) who have not responded adequately to conventional therapy. (1)
- Discontinue LOTRONEX immediately in patients who develop constipation or symptoms of ischemic colitis. Do not resume LOTRONEX in patients who develop ischemic colitis. (2.1, 5.1, 5.2)

1 INDICATIONS AND USAGE

LOTRONEX is a selective serotonin 5-HT3 antagonist indicated only for women with severe diarrhea-predominant irritable bowel syndrome (IBS) who have:

- chronic IBS symptoms (generally lasting 6 months or longer),
- had anatomic or biochemical abnormalities of the gastrointestinal tract excluded, and
- not responded adequately to conventional therapy. (1)

Severe IBS includes diarrhea and 1 or more of the following:

- frequent and severe abdominal pain/discomfort,
- frequent bowel urgency or fecal incontinence,
- disability or restriction of daily activities due to IBS. (1)

2 DOSAGE AND ADMINISTRATION

- Starting dose is 0.5 mg twice a day (2.1)
- May increase dose to 1 mg twice a day after 4 weeks if starting dosage is well tolerated but does not adequately control IBS symptoms (2.1)
- Discontinue LOTRONEX in patients who have not had adequate control of IBS symptoms after 4 weeks of treatment with 1 mg twice a day. (2.1)

3 DOSAGE FORMS AND STRENGTHS

- Tablets: 0.5 and 1 mg (3)

4 CONTRAINDICATIONS

- Do not initiate in patients with constipation (4.1)
- History of chronic or severe constipation or sequelae from constipation; intestinal obstruction, stricture, toxic megacolon, gastrointestinal perforation, and/or adhesions; ischemic colitis; impaired intestinal circulation, thrombophlebitis, or hypercoagulable state; Crohn's disease or ulcerative colitis; diverticulitis; severe hepatic impairment (4.2)
- Concomitant use of fluvoxamine (4.3)

5 WARNINGS AND PRECAUTIONS

- Serious Complications of Constipation: May occur in some patients without warning. Includes obstruction, ileus, impaction, toxic megacolon, and secondary bowel ischemia and in rare cases perforation and death have been reported. Risk is increased in patients who are elderly, debilitated, or taking medications that decrease bowel motility. (5.1)
- Discontinue LOTRONEX immediately if constipation occurs. (5.1)
- Ischemic colitis: May occur in some patients without warning. Promptly evaluate patients with signs of ischemic colitis (e.g., rectal bleeding, bloody diarrhea, new or worsening abdominal pain). (5.2)
- Discontinue LOTRONEX immediately if signs of ischemic colitis occur, such as rectal bleeding, bloody diarrhea, or new or worsening abdominal pain. (5.2)

6 ADVERSE REACTIONS

Most common adverse reactions (incidence >2% and >placebo) in clinical studies were constipation, abdominal discomfort and pain, nausea, and gastrointestinal discomfort and pain. (6.1)

To report SUSPECTED ADVERSE REACTIONS, contact Sebela at 1-844-732-3521 or FDA at 1-800-FDA-1088 orwww.fda.gov/medwatch.

7 DRUG INTERACTIONS

- CYP1A2 inhibitors: Avoid concomitant uses because of increased exposure and half-life of alosetron. Use with fluvoxamine is contraindicated. (4.3, 7.1)
- CYP3A4 inhibitors: Use with caution in combination due to increased exposure of alosetron. (7.2)

8 USE IN SPECIFIC POPULATIONS

- Hepatic impairment: Contraindicated in severe hepatic impairment. Use with caution in patients with mild or moderate hepatic impairment. (4.2, 8.6)
- Geriatric use: Elderly patients may be at greater risk for complications of constipation. (8.5)

FULL PRESCRIBING INFORMATION

WARNING: SERIOUS GASTROINTESTINAL ADVERSE REACTIONS

Infrequent but serious gastrointestinal adverse reactions have been reported with the use of LOTRONEX. These events, including ischemic colitis and serious complications of constipation, have resulted in hospitalization, and rarely, blood transfusion, surgery, and death.

- LOTRONEX is indicated only for women with severe diarrhea-predominant irritable bowel syndrome (IBS) who have not responded adequately to conventional therapy [see Indications and Usage (1)] .
- LOTRONEX should be discontinued immediately in patients who develop constipation or symptoms of ischemic colitis. Patients should immediately report constipation or symptoms of ischemic colitis to their prescriber. LOTRONEX should not be resumed in patients who develop ischemic colitis. Patients who have constipation should immediately contact their prescriber if the constipation does not resolve after LOTRONEX is discontinued. Patients with resolved constipation should resume LOTRONEX only on the advice of their treating prescriber [see Dosage and Administration (2.1), Warnings and Precautions (5.1), (5.2)].

1 INDICATIONS AND USAGE

LOTRONEX is indicated only for women with severe diarrhea-predominant irritable bowel syndrome (IBS) who have:

- chronic IBS symptoms (generally lasting 6 months or longer),
- had anatomic or biochemical abnormalities of the gastrointestinal tract excluded, and
- not responded adequately to conventional therapy.

Diarrhea-predominant IBS is severe if it includes diarrhea and one or more of the following:

- frequent and severe abdominal pain/discomfort,
- frequent bowel urgency or fecal incontinence,
- disability or restriction of daily activities due to IBS.

Because of infrequent but serious gastrointestinal adverse reactions associated with LOTRONEX, the indication is restricted to those patients for whom the benefit-to-risk balance is most favorable.

Clinical studies have not been performed to adequately confirm the benefits of LOTRONEX in men.

2 DOSAGE AND ADMINISTRATION

2.1 Adult Patients

To lower the risk of constipation, LOTRONEX should be started at a dosage of 0.5 mg twice a day. Patients who become constipated at this dosage should stop taking LOTRONEX until the constipation resolves. They may be restarted at 0.5 mg once a day. If constipation recurs at the lower dose, LOTRONEX should be discontinued immediately.

Patients well controlled on 0.5 mg once or twice a day may be maintained on this regimen. If after 4 weeks the dosage is well tolerated but does not adequately control IBS symptoms, then the dosage can be increased to up to 1 mg twice a day . LOTRONEX should be discontinued in patients who have not had adequate control of IBS symptoms after 4 weeks of treatment with 1 mg twice a day.

LOTRONEX can be taken with or without food [see Clinical Pharmacology (12.3)] .

LOTRONEX should be discontinued immediately in patients who develop constipation or signs of ischemic colitis. LOTRONEX should not be restarted in patients who develop ischemic colitis.

Clinical trial and postmarketing experience suggest that debilitated patients or patients taking additional medications that decrease gastrointestinal motility may be at greater risk of serious complications of constipation. Therefore, appropriate caution and follow-up should be exercised if LOTRONEX is prescribed for these patients.

Postmarketing experience suggests that elderly patients may be at greater risk for complications of constipation; therefore, appropriate caution and follow-up should be exercised if LOTRONEX is prescribed for these patients [see Warnings and Precautions (5.1)] .

2.2 Patients with Hepatic Impairment

LOTRONEX is extensively metabolized by the liver, and increased exposure to LOTRONEX is likely to occur in patients with hepatic impairment. Increased drug exposure may increase the risk of serious adverse reactions. LOTRONEX should be used with caution in patients with mild or moderate hepatic impairment and is contraindicated in patients with severe hepatic impairment [see Contraindications (4), Use in Specific Populations (8.6)].

3 DOSAGE FORMS AND STRENGTHS

0.5 mg and 1 mg tablets

LOTRONEX Tablets, 0.5 mg (0.562 mg alosetron HCl equivalent to 0.5 mg alosetron), are white, oval, film-coated tablets debossed with GX EX1 on one face.

LOTRONEX Tablets, 1 mg (1.124 mg alosetron HCl equivalent to 1 mg alosetron), are blue, oval, film-coated tablets debossed with GX CT1 on one face.

4 CONTRAINDICATIONS

4.1 Constipation

LOTRONEX should not be initiated in patients with constipation [see Warnings and Precautions (5.1)] .

4.2 History of Severe Bowel or Hepatic Disorders

LOTRONEX is contraindicated in patients with a history of the following:

- chronic or severe constipation or sequelae from constipation
- intestinal obstruction, stricture, toxic megacolon, gastrointestinal perforation, and/or adhesions
- ischemic colitis, impaired intestinal circulation, thrombophlebitis, or hypercoagulable state
- Crohn's disease or ulcerative colitis
- diverticulitis
- severe hepatic impairment

4.3 Concomitant Use of Fluvoxamine

Concomitant administration of LOTRONEX with fluvoxamine is contraindicated. Fluvoxamine, a known strong inhibitor of CYP1A2, has been shown to increase mean alosetron plasma concentrations (AUC) approximately 6-fold and prolong the half-life by approximately 3-fold [see Drug Interactions (7.1)] .

5 WARNINGS AND PRECAUTIONS

5.1 Serious Complications of Constipation

Some patients have experienced serious complications of constipation without warning.

Serious complications of constipation, including obstruction, ileus, impaction, toxic megacolon, and secondary bowel ischemia, have been reported with use of LOTRONEX during clinical trials. Complications of constipation have been reported with use of 1 mg twice daily and with lower doses. A dose response relationship has not been established for serious complications of constipation. The incidence of serious complications of constipation was approximately 0.1% (1 per 1,000 patients) in women receiving either LOTRONEX or placebo. In addition, rare cases of perforation and death have been reported from postmarketing clinical practice. In some cases, complications of constipation required intestinal surgery, including colectomy. Patients who are elderly, debilitated, or taking additional medications that decrease gastrointestinal motility may be at greater risk for complications of constipation.

LOTRONEX should be discontinued immediately in patients who develop constipation [see Boxed Warning].

5.2 Ischemic Colitis

Some patients have experienced ischemic colitis without warning.

Ischemic colitis has been reported in patients receiving LOTRONEX in clinical trials as well as during marketed use of the drug. In IBS clinical trials, the cumulative incidence of ischemic colitis in women receiving LOTRONEX was 0.2% (2 per 1,000 patients, 95% confidence interval 1 to 3) through 3 months and was 0.3% (3 per 1,000 patients, 95% confidence interval 1 to 4) through 6 months. Ischemic colitis has been reported with use of 1 mg twice daily and with lower doses. A dose-response relationship has not been established. Ischemic colitis was reported in one patient receiving placebo. The patient experience in controlled clinical trials is insufficient to estimate the incidence of ischemic colitis in patients taking LOTRONEX for longer than 6 months.

LOTRONEX should be discontinued immediately in patients with signs of ischemic colitis such as rectal bleeding, bloody diarrhea, or new or worsening abdominal pain. Because ischemic colitis can be life-threatening, patients with signs or symptoms of ischemic colitis should be evaluated promptly and have appropriate diagnostic testing performed. Treatment with LOTRONEX should not be resumed in patients who develop ischemic colitis.

6 ADVERSE REACTIONS

The following adverse reactions are described in more detail in other sections of the label:

- Complications of constipation [see Boxed Warning, Warnings and Precautions (5.1)]
- Ischemic colitis [see Boxed Warning, Warnings and Precautions (5.2)]

6.1 Clinical Trials Experience

Because clinical trials are conducted under widely varying conditions, adverse reaction rates observed in the clinical trials of a drug cannot be directly compared to rates in the clinical trials of another drug and may not reflect the rates observed in practice.

Patients with Irritable Bowel Syndrome: Table 1 summarizes adverse reactions from 22 repeat-dose studies in patients with IBS who were treated with 1 mg of LOTRONEX twice daily for 8 to 24 weeks. The adverse reactions in Table 1 were reported in 1% or more of patients who received LOTRONEX and occurred more frequently on LOTRONEX than on placebo. A statistically significant difference was observed for constipation in patients treated with LOTRONEX compared to placebo (p<0.0001).

Table 1. Adverse Reactions Reported in ≥1% of Patients with Irritable Bowel Syndrome and More Frequently on LOTRONEX 1 mg Twice Daily Than Placebo
 |  | LOTRONEX
Body System | Placebo | 1 mg twice daily
Adverse Reaction | (n = 2,363) | (n = 8,328)
Gastrointestinal
Constipation | 6% | 29%
Abdominal discomfort and pain | 4% | 7%
Nausea | 5% | 6%
Gastrointestinal discomfort and pain | 3% | 5%
Abdominal distention | 1% | 2%
Regurgitation and reflux | 2% | 2%
Hemorrhoids | 1% | 2%

Gastrointestinal: Constipation is a frequent and dose-related side effect of treatment with LOTRONEX [see Warnings and Precautions (5.1)] . In clinical studies constipation was reported in approximately 29% of patients with IBS treated with LOTRONEX 1 mg twice daily (n = 9,316). This effect was statistically significant compared to placebo (p<0.0001). Eleven percent (11%) of patients treated with LOTRONEX 1 mg twice daily withdrew from the studies due to constipation. Although the number of patients with IBS treated with LOTRONEX 0.5 mg twice daily is relatively small (n = 243), only 11% of those patients reported constipation and 4% withdrew from clinical studies due to constipation. Among the patients treated with LOTRONEX 1 mg twice daily who reported constipation, 75% reported a single episode and most reports of constipation (70%) occurred during the first month of treatment, with the median time to first report of constipation onset of 8 days. Occurrences of constipation in clinical trials were generally mild to moderate in intensity, transient in nature, and resolved either spontaneously with continued treatment or with an interruption of treatment. However, serious complications of constipation have been reported in clinical studies and in postmarketing experience [see Boxed Warning and Warnings and Precautions (5.1)] . In Studies 1 and 2, 9% of patients treated with LOTRONEX reported constipation and 4 consecutive days with no bowel movement [see Clinical Studies (14.2)] . Following interruption of treatment, 78% of the affected patients resumed bowel movements within a 2-day period and were able to re-initiate treatment with LOTRONEX.

Hepatic: A similar incidence in elevation of ALT (>2-fold) was seen in patients receiving LOTRONEX or placebo (1.0% vs. 1.2%). A single case of hepatitis (elevated ALT, AST, alkaline phosphatase, and bilirubin) without jaundice in a patient receiving LOTRONEX was reported in a 12-week study. A causal association with LOTRONEX has not been established.

Long-Term Safety: Patient experience in controlled clinical trials is insufficient to estimate the incidence of ischemic colitis in patients taking LOTRONEX for longer than 6 months.

Women with Severe Diarrhea-Predominant Irritable Bowel Syndrome: Table 2 summarizes the gastrointestinal adverse reactions from 1 repeat-dose study in female patients with severe diarrhea-predominant IBS who were treated for 12 weeks. The adverse reactions in Table 2 were reported in 3% or more of patients who received LOTRONEX and occurred more frequently with LOTRONEX than with placebo. Other events reported in 3% or more of patients who received LOTRONEX and occurring more frequently with LOTRONEX than with placebo included upper respiratory tract infection, viral gastroenteritis, muscle spasms, headaches, and fatigue.

Table 2. Gastrointestinal Adverse Reactions Reported in ≥3% of Women with Severe Diarrhea-Predominant Irritable Bowel Syndrome and More Frequently on LOTRONEX Than Placebo.
 |  | LOTRONEX | LOTRONEX | LOTRONEX
Adverse Reaction | Placebo | 0.5 mg once daily | 1 mg once daily | 1 mg twice daily
 | (n = 176) | (n = 175) | (n = 172) | (n = 176)
Constipation | 5% | 9% | 16% | 19%
Abdominal pain | 3% | 5% | 6% | 7%
Diarrhea | 2% | 3% | 2% | 2%
Hemorrhoidal hemorrhage | 2% | 3% | 2% | 2%
Flatulance | 2% | 2% | 1% | 3%
Hemorrhoids | 2% | 1% | 1% | 3%
Abdominal pain upper | 1% | 3% | 1% | 1%

Adverse reactions reported in another study of 701 women with severe diarrhea-predominant IBS were similar to those shown in Table 2. Gastrointestinal adverse reactions reported in 3% or more of patients who received LOTRONEX and occurring more frequently with LOTRONEX than with placebo included constipation (14% and 10% of patients taking LOTRONEX 1 mg twice daily or 0.5 mg as needed, respectively, compared with 2% taking placebo), abdominal pain, nausea, vomiting, and flatulence. Other events reported in 3% or more of patients who received LOTRONEX and occurring more frequently with LOTRONEX than with placebo included nasopharyngitis, sinusitis, upper respiratory tract infection, urinary tract infection, viral gastroenteritis, and cough.

Constipation: Constipation was the most frequent adverse reaction among women with severe diarrhea-predominant IBS represented in Table 2. There was a dose response in the groups treated with LOTRONEX in the number of patients withdrawn due to constipation (2% on placebo, 5% on 0.5 mg once daily, 8% on 1 mg once daily, and 11% on 1 mg twice daily). Among these patients with severe diarrhea-predominant IBS treated with LOTRONEX who reported constipation most (75%) reported one episode which occurred within the first 15 days of treatment and persisted for 4 to 5 days.

Other Events Observed During Clinical Evaluation of LOTRONEX: During its assessment in clinical trials, multiple and single doses of LOTRONEX were administered, resulting in 11,874 subject exposures in 86 completed clinical studies. The conditions, dosages, and duration of exposure to LOTRONEX varied between trials, and the studies included healthy male and female volunteers as well as male and female patients with IBS and other indications.

In the listing that follows, reported adverse reactions were classified using a standardized coding dictionary. Only those events that an investigator believed were possibly related to LOTRONEX, occurred in at least 2 patients, and occurred at a greater frequency during treatment with LOTRONEX than during placebo administration are presented. Serious adverse reactions occurring in at least 1 patient for whom an investigator believed there was reasonable possibility that the event was related to treatment with LOTRONEX and occurring at a greater frequency in patients treated with LOTRONEX than placebo-treated patients are also presented.

In the following listing, events are categorized by body system. Within each body system, events are presented in descending order of frequency. The following definitions are used: infrequent adverse reactions are those occurring on one or more occasion in 1/100 to 1/1,000 patients; rare adverse reactions are those occurring on one or more occasion in fewer than 1/1,000 patients.

Although the events reported occurred during treatment with LOTRONEX, they were not necessarily caused by it.

- Blood and Lymphatic: Rare: Quantitative red cell or hemoglobin defects, and hemorrhage.
- Cardiovascular: Infrequent: Tachyarrhythmias. Rare: Arrhythmias, increased blood pressure, and extrasystoles.
- Drug Interaction, Overdose, and Trauma: Rare: Contusions and hematomas.
- Ear, Nose, and Throat: Rare: Ear, nose, and throat infections; viral ear, nose, and throat infections; and laryngitis.
- Endocrine and Metabolic: Rare: Disorders of calcium and phosphate metabolism, hyperglycemia, hypothalamus/pituitary hypofunction, hypoglycemia, and fluid disturbances.
- Eye: Rare: Light sensitivity of eyes.
- Gastrointestinal: Infrequent: Hyposalivation, dyspeptic symptoms, gastrointestinal spasms, ischemic colitis [see Warnings and Precautions (5.2)] , and gastrointestinal lesions. Rare: Abnormal tenderness, colitis, gastrointestinal signs and symptoms, proctitis, diverticulitis, positive fecal occult blood, hyperacidity, decreased gastrointestinal motility and ileus, gastrointestinal obstructions, oral symptoms, gastrointestinal intussusception, gastritis, gastroduodenitis, gastroenteritis, and ulcerative colitis.
- Hepatobiliary Tract and Pancreas: Rare: Abnormal bilirubin levels and cholecystitis.
- Lower Respiratory: Infrequent: Breathing disorders.
- Musculoskeletal: Rare: Muscle pain; muscle stiffness, tightness and rigidity; and bone and skeletal pain.
- Neurological: Infrequent: Hypnagogic effects. Rare: Memory effects, tremors, dreams, cognitive function disorders, disturbances of sense of taste, disorders of equilibrium, confusion, sedation, and hypoesthesia.
- Non-Site Specific: Infrequent: Malaise and fatigue, cramps, pain, temperature regulation disturbances. Rare: Burning sensations, hot and cold sensations, cold sensations, and fungal infections.
- Psychiatry: Infrequent: Anxiety. Rare: Depressive moods.
- Reproduction: Rare: Sexual function disorders, female reproductive tract bleeding and hemorrhage, reproductive infections, and fungal reproductive infections.
- Skin: Infrequent: Sweating and urticaria. Rare: Hair loss and alopecia; acne and folliculitis; disorders of sweat and sebum; allergic skin reaction; eczema; skin infections; dermatitis and dermatosis; and nail disorders.
- Urology: Infrequent: Urinary frequency. Rare: Bladder inflammation; polyuria and diuresis; and urinary tract hemorrhage.

6.2 Postmarketing Experience

In addition to events reported in clinical trials, the following events have been identified during use of LOTRONEX in clinical practice. Because they were reported voluntarily from a population of unknown size, estimates of frequency cannot be made. These events have been chosen for inclusion due to a combination of their seriousness, frequency of reporting, or potential causal connection to LOTRONEX.

- Gastrointestinal: Impaction, perforation, ulceration, small bowel mesenteric ischemia.
- Neurological: Headache.
- Skin: Rash.

7 DRUG INTERACTIONS

In vivo data suggest that alosetron is primarily metabolized by cytochrome P450 (CYP) 1A2, with minor contributions from CYP3A4 and CYP2C9. Therefore, inducers or inhibitors of these enzymes may change the clearance of alosetron.

7.1 CYP1A2 Inhibitors

Fluvoxamine is a known strong inhibitor of CYP1A2 and also inhibits CYP3A4, CYP2C9, and CYP2C19. In a pharmacokinetic study, 40 healthy female subjects received fluvoxamine in escalating doses from 50 to 200 mg/ day for 16 days, with coadministration of alosetron 1 mg on the last day. Fluvoxamine increased mean alosetron plasma concentrations (AUC) approximately 6-fold and prolonged the half-life by approximately 3-fold. Concomitant administration of alosetron and fluvoxamine is contraindicated [see Contraindications (4.3)] .

Concomitant administration of alosetron and moderate CYP1A2 inhibitors, including quinolone antibiotics and cimetidine, has not been evaluated, but should be avoided unless clinically necessary because of similar potential drug interactions.

7.2 CYP3A4 Inhibitors

Ketoconazole is a known strong inhibitor of CYP3A4. In a pharmacokinetic study, 38 healthy female subjects received ketoconazole 200 mg twice daily for 7 days, with coadministration of alosetron 1 mg on the last day. Ketoconazole increased mean alosetron plasma concentrations (AUC) by 29%. Caution should be used when alosetron and ketoconazole are administered concomitantly. Coadministration of alosetron and strong CYP3A4 inhibitors such as clarithromycin, telithromycin, protease inhibitors, voriconazole, and itraconazole has not been evaluated but should be undertaken with caution because of similar potential drug interactions. The effect of induction or inhibition of other pathways on exposure to alosetron and its metabolites is not known.

7.3 Other CYP Enzymes

In vitro human liver microsome studies and an in vivo metabolic probe study demonstrated that alosetron did not inhibit CYP enzymes 3A4, 2C9, or 2C19. In vitro at total drug concentrations 27-fold higher than peak plasma concentrations observed with the 1 mg dose, alosetron inhibited CYP enzymes 1A2 (60%) and 2E1 (50%). In an in vivo metabolic probe study, alosetron did not inhibit CYP2E1 but did produce 30% inhibition of both CYP1A2 and N-acetyltransferase. Although not studied with alosetron, inhibition of N-acetyltransferase may have clinically relevant consequences for drugs such as isoniazid, procainamide, and hydralazine. The effect on CYP1A2 was explored further in a clinical interaction study with theophylline and no effect on metabolism was observed. Another study showed that alosetron had no clinically significant effect on plasma concentrations of the oral contraceptive agents ethinyl estradiol and levonorgestrel (CYP3A4 substrates). A clinical interaction study was also conducted with alosetron and the CYP3A4 substrate cisapride. No significant effects on cisapride metabolism or QT interval were noted. The effects of alosetron on monoamine oxidases and on intestinal first pass secondary to high intraluminal concentrations have not been examined. Based on the above data from in vitro and in vivo studies, it is unlikely that alosetron will inhibit the hepatic metabolic clearance of drugs metabolized by the CYP enzymes 2C9, 2C19, or 2E1.

Alosetron does not appear to induce the major cytochrome P450 drug-metabolizing enzyme 3A. Alosetron also does not appear to induce CYP enzymes 2E1 or 2C19. It is not known whether alosetron might induce other enzymes.

8 USE IN SPECIFIC POPULATIONS

8.1 Pregnancy

Risk Summary

The available data with LOTRONEX use in pregnant women are insufficient to draw conclusions about any drug-associated risks for major birth defects, miscarriage, or adverse maternal or fetal outcomes. In animal reproduction studies, no adverse developmental effects were observed with oral administration of alosetron in rats and rabbits during organogenesis at doses 160 to 240 times, respectively, the recommended human dosage (see Data).

The estimated background risk of major birth defects and miscarriage for the indicated populations is unknown. All pregnancies have a background risk of birth defect, loss, or other adverse outcomes. In the U.S. general population, the estimated background risk of major birth defects and miscarriage in clinically recognized pregnancies is 2 to 4% and miscarriage is 15 to 20%, respectively.

Data

Animal Data

No adverse developmental effects were observed with oral administration of alosetron during the period of organogenesis to pregnant rats at doses up to 40 mg/kg/day (about 160 times the recommended human dose based on body surface area) or to pregnant rabbits at doses up to 30 mg/kg/day (about 240 times the recommended daily human dose based on body surface area).

8.2 Lactation

Alosetron and/or metabolites of alosetron are excreted in the breast milk of lactating rats. It is not known whether alosetron is excreted in human milk. Because many drugs are excreted in human milk, caution should be exercised when LOTRONEX is administered to a nursing woman.

Risk Summary

There are no data regarding the presence of alosetron in human milk, the effects on the breastfed infant, or the effects on milk production.

Alosetron and/or metabolites of alosetron are present in the breast milk of lactating rats. When a drug is present in animal milk, it is likely that the drug will be present in human milk. The developmental and health benefits of breastfeeding should be considered along with the mother’s clinical need for LOTRONEX and any potential adverse effects on the breastfed infant from LOTRONEX or from the underlying maternal condition.

Clinical Considerations

Monitor infants exposed to LOTRONEX through breast milk for severe constipation and blood in stools.

8.4 Pediatric Use

Safety and effectiveness in pediatric patients have not been established. Use of LOTRONEX is not recommended in the pediatric population, based upon the risk of serious complications of constipation and ischemic colitis in adults.

8.5 Geriatric Use

In some studies in healthy men or women, plasma concentrations were elevated by approximately 40% in individuals 65 years and older compared to young adults [see Warnings and Precautions (5.1)] . However, this effect was not consistently observed in men.

Postmarketing experience suggests that elderly patients may be at greater risk for complications of constipation therefore, appropriate caution and follow-up should be exercised if LOTRONEX is prescribed for these patients [see Warnings and Precautions (5.1)] .

8.6 Hepatic Impairment

Due to the extensive hepatic metabolism of alosetron, increased exposure to alosetron and/or its metabolites is likely to occur in patients with hepatic impairment. Alosetron should not be used in patients with severe hepatic impairment and should be used with caution in patients with mild or moderate hepatic impairment.

A single 1 mg oral dose of alosetron was administered to 1 female and 5 male patients with moderate hepatic impairment (Child-Pugh score of 7 to 9) and to 1 female and 2 male patients with severe hepatic impairment (Child-Pugh score of >9). In comparison with historical data from healthy subjects, patients with severe hepatic impairment displayed higher systemic exposure to alosetron. The female with severe hepatic impairment displayed approximately 14-fold higher exposure, while the female with moderate hepatic impairment displayed approximately 1.6-fold higher exposure, than healthy females. Due to the small number of subjects and high intersubject variability in the pharmacokinetic findings, no definitive quantitative conclusions can be made. However, due to the greater exposure to alosetron in the female with severe hepatic impairment, alosetron should not be used in females with severe hepatic impairment [see Dosage and Administration (2.2), Contraindications (4)] .

8.7 Renal Impairment

Renal impairment (creatinine clearance 4 to 56 mL/min) has no effect on the renal elimination of alosetron due to the minor contribution of this pathway to elimination. The effect of renal impairment on metabolite pharmacokinetics and the effect of end-stage renal disease have not been assessed.

10 OVERDOSAGE

There is no specific antidote for overdose of LOTRONEX. Patients should be managed with appropriate supportive therapy. Individual oral doses as large as 16 mg have been administered in clinical studies without significant adverse reactions. This dose is 8 times higher than the recommended total daily dose. Inhibition of the metabolic elimination and reduced first pass of other drugs might occur with overdoses of LOTRONEX [see Drug Interactions (7)].

11 DESCRIPTION

The active ingredient in LOTRONEX Tablets is alosetron hydrochloride (HCl), a potent and selective antagonist of the serotonin 5-HT3 receptor type. Chemically, alosetron is designated as 2,3,4,5-tetrahydro-5-methyl-2-[(5-methyl-1H-imidazol-4-yl)methyl]-1H-pyrido[4,3-b]indol-1-one, monohydrochloride. Alosetron is achiral and has the empirical formula C17H18N4O•HCl, representing a molecular weight of 330.8. Alosetron is a white to beige solid that has a solubility of 61 mg/mL in water, 42 mg/mL in 0.1M hydrochloric acid, 0.3 mg/mL in pH 6 phosphate buffer, and <0.1 mg/mL in pH 8 phosphate buffer. The chemical structure of alosetron is:

LOTRONEX Tablets are supplied for oral administration as 0.5 mg (white) and 1 mg (blue) tablets. The 0.5 mg tablet contains 0.562 mg alosetron HCl equivalent to 0.5 mg alosetron, and the 1 mg tablet contains 1.124 mg alosetron HCl equivalent to 1 mg of alosetron. Each tablet also contains the inactive ingredients lactose (anhydrous), magnesium stearate, microcrystalline cellulose, and pregelatinized starch. The white film coat for the 0.5 mg tablet contains hypromellose, titanium dioxide, and triacetin. The blue film coat for the 1 mg tablet contains hypromellose, titanium dioxide, triacetin, and indigo carmine.

12 CLINICAL PHARMACOLOGY

12.1 Mechanism of Action

Alosetron is a potent and selective 5-HT3 receptor antagonist. 5-HT3 receptors are ligand-gated cation channels that are extensively distributed on enteric neurons in the human gastrointestinal tract, as well as other peripheral and central locations. Activation of these channels and the resulting neuronal depolarization affect the regulation of visceral pain, colonic transit, and gastrointestinal secretions, processes that relate to the pathophysiology of IBS. 5-HT3 receptor antagonists such as alosetron inhibit activation of non-selective cation channels, which results in the modulation of the enteric nervous system.

The cause of IBS is unknown. IBS is characterized by visceral hypersensitivity and hyperactivity of the gastrointestinal tract, which lead to abnormal sensations of pain and motor activity. Following distention of the rectum, patients with IBS exhibit pain and discomfort at lower volumes than healthy volunteers. Following such distention, alosetron reduced pain and exaggerated motor responses, possibly due to blockade of 5-HT3 receptors.

12.2 Pharmacodynamics

In healthy volunteers and patients with IBS, alosetron (2 mg orally, twice daily for 8 days) increased colonic transit time without affecting orocecal transit time. In healthy volunteers, alosetron also increased basal jejunal water and sodium absorption after a single 4 mg dose. In patients with IBS, multiple oral dosages of alosetron (4 mg twice daily for 6.5 days) significantly increased colonic compliance.

Single oral doses of alosetron administered to healthy men produced a dose-dependent reduction in the flare response seen after intradermal injection of serotonin. Urinary 6-β-hydroxycortisol excretion decreased by 52% in elderly subjects after 27.5 days of alosetron 2 mg administered orally twice daily. This decrease was not statistically significant. In another study utilizing alosetron 1 mg administered orally twice daily for 4 days, there was a significant decrease in urinary 6-β-hydroxycortisol excretion. However, there was no change in the ratio of 6-β-hydroxycortisol to cortisol, indicating a possible decrease in cortisol production. The clinical significance of these findings is unknown.

12.3 Pharmacokinetics

The pharmacokinetics of alosetron have been studied after single oral doses ranging from 0.05 to 16 mg in healthy men. The pharmacokinetics of alosetron have also been evaluated in healthy women and men and in patients with IBS after repeated oral dosages ranging from 1 mg twice daily to 8 mg twice daily.

Absorption: Alosetron was rapidly absorbed after oral administration with a mean absolute bioavailability of approximately 50% to 60% (approximate range, 30% to >90%). After administration of radiolabeled alosetron, only 1% of the dose was recovered in the feces as unchanged drug. Following oral administration of a 1 mg alosetron dose to young men, a peak plasma concentration of approximately 5 ng/mL occurred at 1 hour. In young women, the mean peak plasma concentration was approximately 9 ng/mL, with a similar time to peak.

Plasma concentrations were 30% to 50% lower and less variable in men compared to women given the same oral dose. Population pharmacokinetic analysis in IBS patients confirmed that alosetron concentrations were influenced by gender (27% lower in men).

Food Effects: Alosetron absorption is decreased by approximately 25% by co-administration with food, with a mean delay in time to peak concentration of 15 minutes [see Dosage and Administration (2.1)] .

Distribution: Alosetron demonstrates a volume of distribution of approximately 65 to 95 L. Plasma protein binding is 82% over a concentration range of 20 to 4,000 ng/mL.

Metabolism and Elimination: Plasma concentrations of alosetron increase proportionately with increasing single oral doses up to 8 mg and more than proportionately at a single oral dose of 16 mg. Twice-daily oral dosing of alosetron does not result in accumulation. The terminal elimination half-life of alosetron is approximately 1.5 hours (plasma clearance is approximately 600 mL/min). Population pharmacokinetic analysis in patients with IBS confirmed that alosetron clearance is minimally influenced by doses up to 8 mg.

Renal elimination of unchanged alosetron accounts for only 13% of the dose. Renal clearance is approximately 112 mL/min.

A study with^14C-labeled alosetron in Caucasian males (n = 3) and females (n = 3) and an Asian male (n = 1) showed similar serum metabolite profiles. Unchanged alosetron was the major component in serum, with other metabolites being present at low concentrations, none amounting to more than 15% of the unmetabolized alosetron concentration. The circulating metabolites were identified as 6-hydroxy glucuronide, 6-hydroxy sulphate, 7-hydroxy sulphate, hydroxymethyl imidazole, and mono- and bis-oxygenated imidazole derivatives of alosetron. The metabolites are unlikely to contribute to the biological activity of alosetron. Of the circulating Phase I metabolites, only the hydroxymethyl imidazole has weak pharmacological activity, around 10-fold less potent than alosetron. Total recovery of radioactivity in the excreta was 85 ± 6%. The majority of the radiolabeled dose is excreted in the urine (74 ± 5%). The major urinary metabolites were the 6-hydroxy glucuronide and the mono- and bis-oxygenated imidazole derivatives of alosetron. 11 ± 4% of the radiolabeled dose was excreted in the feces with less than 1% of the dose being excreted as the unchanged alosetron.

Alosetron is metabolized by human microsomal cytochrome P450 (CYP), shown in vitro to involve enzymes 2C9 (30%), 3A4 (18%), and 1A2 (10%). Non–CYP-mediated Phase I metabolic conversion also contributes to an extent of about 11%. However, in vivo data suggest that CYP1A2 plays a more prominent role in alosetron metabolism (62 to 97% of alosetron clearance) based on correlation of alosetron clearance with in vivo CYP1A2 activity measured by probe substrate, increased clearance induced by smoking, and inhibition of clearance by fluvoxamine [see Contraindications (4), Drug Interactions (7)].

13 NONCLINICAL TOXICOLOGY

13.1 Carcinogenesis, Mutagenesis, Impairment of Fertility

In 2-year oral studies, alosetron was not carcinogenic in mice at doses up to 30 mg/kg/day or in rats at doses up to 40 mg/kg/day. These doses are about 60 to 160 times, respectively, the recommended human dose of alosetron of 2 mg/day (1 mg twice daily) based on body surface area. Alosetron was not genotoxic in the Ames tests, the mouse lymphoma cell (L5178Y/TK±) forward gene mutation test, the human lymphocyte chromosome aberration test, the ex vivo rat hepatocyte unscheduled DNA synthesis (UDS) test, or the in vivo rat micronucleus test for mutagenicity. Alosetron at oral doses up to 40 mg/kg/day (about 160 times the recommended daily human dose based on body surface area) was found to have no effect on fertility and reproductive performance of male or female rats.

14 CLINICAL STUDIES

14.1 Dose-Ranging Study

Data from a dose-ranging study of women (n = 85) who received LOTRONEX 0.5 mg twice daily indicated that the incidence of constipation (14%) was lower than that experienced by women receiving 1 mg twice daily (29%). Therefore, to lower the risk of constipation, LOTRONEX should be started at a dosage of 0.5 mg twice a day. The efficacy of the 0.5 mg twice-daily dosage in treating severe diarrhea-predominant IBS has not been adequately evaluated in clinical trials. [See Dosage and Administration (2.1)]

14.2 Efficacy Studies

LOTRONEX has been studied in women with IBS in five 12-week US multicenter, randomized, double-blind, placebo-controlled clinical studies.

Table 3. Efficacy Studies Conducted in Women With Irritable Bowel Syndrome (IBS)
Study | Patient Population | Placebo; (n) | Lotronex Dose; (n)
1 and 2 | Non-constipated women with IBS | (640) | 1 mg twice daily; (633)
3 and 4 | Women with severe diarrhea-predominant; IBS (defined as bowel urgency ≥50% of days) | (515) | 1 mg twice daily; (778)
5 | Women with severe diarrhea-predominant; IBS (defined as average pain ≥moderate,; urgency ≥50% of days, and/or restriction of; daily activities ≥25% of days) | (176) | 0.5 mg once daily (177)
 | Women with severe diarrhea-predominant; IBS (defined as average pain ≥moderate,; urgency ≥50% of days, and/or restriction of; daily activities ≥25% of days) | (176) | 1 mg once daily (175)
 | Women with severe diarrhea-predominant; IBS (defined as average pain ≥moderate,; urgency ≥50% of days, and/or restriction of; daily activities ≥25% of days) | (176) | 1 mg once daily (177)

Studies in Non-Constipated Women with Irritable Bowel Syndrome: Studies 1 and 2 were conducted in non-constipated women with IBS meeting the Rome Criteria^1 for at least 6 months. Women with severe pain or a history of severe constipation were excluded. A 2-week run-in period established baseline IBS symptoms.

About two thirds of the women had diarrhea-predominant IBS. Compared with placebo, 10% to 19% more women with diarrhea-predominant IBS who received LOTRONEX had adequate relief of IBS abdominal pain and discomfort during each month of the study.

Studies in Women With Severe Diarrhea-Predominant Irritable Bowel Syndrome: LOTRONEX is indicated only for women with severe diarrhea-predominant IBS [see Indications and Usage (1)] . The efficacy of LOTRONEX in this subset of the women studied in clinical trials is supported by prospective and retrospective analyses.

Prospective Analyses: Studies 3 and 4 were conducted in women with diarrhea-predominant IBS and bowel urgency on at least 50% of days at entry. Women receiving LOTRONEX had significant increases over placebo (13% to 16%) in the median percentage of days with urgency control.

The lower gastrointestinal functions of stool consistency, stool frequency, and sense of incomplete evacuation were also evaluated by patients' daily reports. Stool consistency was evaluated on a scale of 1 to 5 (1 = very hard, 2 = hard, 3 = formed, 4 = loose, and 5 = watery). At baseline, average stool consistency was approximately 4 (loose) for both treatment groups. During the 12 weeks of treatment, the average stool consistency decreased to approximately 3.0 (formed) for patients who received LOTRONEX and 3.5 for the patients who received placebo in the 2 studies.

At baseline, average stool frequency was approximately 3.2 per day for both treatment groups. During the 12 weeks of treatment, the average daily stool frequency decreased to approximately 2.1 and 2.2 for patients receiving LOTRONEX and 2.7 and 2.8 for patients receiving placebo in the 2 studies.

There was no consistent effect upon the sense of incomplete evacuation during the 12 weeks of treatment for patients receiving LOTRONEX as compared to patients receiving placebo in either study.

Study 5 was conducted in women with severe diarrhea-predominant IBS and 1 or more of the following: frequent and severe abdominal pain or discomfort, frequent bowel urgency or fecal incontinence, disability or restriction of daily activities due to IBS. To evaluate the proportion of patients who responded to treatment, patients were asked every 4 weeks to compare their IBS symptoms during the previous month of treatment with how they usually felt during the 3 months prior to the study using an ordered 7-point scale (substantially worse to substantially improved). A responder was defined as a subject who reported moderate or substantial improvement on this global improvement scale (GIS). At Week 12, all three groups receiving LOTRONEX had significantly greater percentages of GIS responders compared to the placebo group (43% to 51% vs. 31%) using a Last Observation Carried Forward (LOCF) analysis. It should be noted that approximately 4% of subjects in each LOTRONEX dose group who were classified as responders using this approach were observed only through week 4. At each of the 4 week intervals of the treatment phase, all three dosages of LOTRONEX provided improvement in the average adequate relief rate of IBS pain and discomfort, stool consistency, stool frequency, and sense of urgency compared with placebo.

Retrospective Analyses: In analyses of patients from Studies 1 and 2 who had diarrhea-predominant IBS and indicated their baseline run-in IBS symptoms were severe at the start of the trial, LOTRONEX provided greater adequate relief of IBS pain and discomfort than placebo. In further analyses of Studies 1 and 2, 57% of patients had urgency at baseline on 5 or more days per week. In this subset, 32% of patients on LOTRONEX had urgency no more than 1 day in the last week of the trial, compared with 19% of patients on placebo.

In Studies 3 and 4, 66% of patients had urgency at baseline on 5 or more days per week. In this subset, 50% of patients on LOTRONEX had urgency no more than 1 day in the last week of the trial, compared with 29% of patients on placebo. Moreover, in the same subset, 12% on LOTRONEX had urgency no more than 2 days per week in any of the 12 weeks on treatment compared with 1% of placebo patients.

In Studies 1 and 2, patient-reported subjective outcomes related to IBS were assessed by questionnaires obtained at baseline and week 12. Patients in the more severe subset who received LOTRONEX reported less difficulty sleeping, less tiredness, fewer eating problems, and less interference with social activities and work/main activities due to IBS symptoms or problems compared to those who received placebo. Change in the impact of IBS symptoms and problems on emotional and mental distress and on physical and sexual activity in women who received LOTRONEX were not statistically different from those reported by women who received placebo.

14.3 Long-Term Use

In a 48-week multinational, double-blind, placebo-controlled study, LOTRONEX 1 mg twice daily was evaluated in 714 women with non-constipated IBS. A retrospective analysis of the subset of women with severe diarrhea-predominant IBS (urgency on at least 10 days during the 2-week baseline period) was performed. Of the 417 patients with severe diarrhea-predominant IBS, 62% completed the trial.

LOTRONEX (n = 198) provided a greater average rate of adequate relief of IBS pain and discomfort (52% vs. 41%) and a greater average rate of satisfactory control of bowel urgency (60% vs. 48%) compared with placebo (n = 219). Significant improvement of these symptoms occurred for most of the 48-week treatment period with no evidence of tachyphylaxis.

15 REFERENCES

1. Thompson WG, Creed F, Drossman DA, et al. Functional bowel disease and functional abdominal pain. Gastroenterol Int. 1992;5:75-91.

16 HOW SUPPLIED/STORAGE AND HANDLING

LOTRONEX Tablets, 0.5 mg (0.562 mg alosetron HCl equivalent to 0.5 mg alosetron) are white, oval, film-coated tablets debossed with GX EX1 on one face.

Bottles of 30 (NDC 65483-894-03) with child-resistant closures.

LOTRONEX Tablets, 1 mg (1.124 mg alosetron HCl equivalent to 1 mg alosetron), are blue, oval, film-coated tablets debossed with GX CT1 on one face.

Bottles of 30 (NDC 65483-895-03) with child-resistant closures.

Store at 20-25°C (68-77°F) (USP Controlled Room Temperature). Protect from light and moisture.

17 PATIENT COUNSELING INFORMATION

Advise the patient to read the FDA-approved labeling (Medication Guide).

Prescriber and Patient Responsibilities

Patients should be fully counseled on and understand the risks and benefits of LOTRONEX before an initial prescription is written. The patient may be educated by the prescriber or a healthcare provider under a prescriber's direction. Patients should be fully counseled on and understand the risks and benefits of LOTRONEX before an initial prescription is written. The patient may be educated by the prescriber or a healthcare provider under a prescriber's direction.

Prescribers must:

- counsel patients for whom LOTRONEX is appropriate about the benefits and risks of LOTRONEX and discuss the impact of IBS symptoms on the patient's life.counsel patients for whom LOTRONEX is appropriate about the benefits and risks of LOTRONEX and discuss the impact of IBS symptoms on the patient's life.
- review the Medication Guide, which outlines the benefits and risks of LOTRONEX, and instruct the patient to read it carefully. Answer all questions the patient may have about LOTRONEX. The complete text of the Medication Guide is printed at the end of this document.review the Medication Guide, which outlines the benefits and risks of LOTRONEX, and instruct the patient to read it carefully. Answer all questions the patient may have about LOTRONEX. The complete text of the Medication Guide is printed at the end of this document.
- provide each patient with appropriate instructions for taking LOTRONEX.provide each patient with appropriate instructions for taking LOTRONEX.

Additional copies of the Medication Guide are available by contacting Sebela at 1-844-732-3521 or visiting wwwlotronex.com.

Patients who are prescribed LOTRONEX should be instructed to:

- read the Medication Guide before starting LOTRONEX and each time they refill their prescription.read the Medication Guide before starting LOTRONEX and each time they refill their prescription.
- not start taking LOTRONEX if they are constipated.not start taking LOTRONEX if they are constipated.
- immediately discontinue LOTRONEX and contact their prescriber if they become constipated, or have symptoms of ischemic colitis such as new or worsening abdominal pain, bloody diarrhea, or blood in the stool. Contact their prescriber again if their constipation does not resolve after discontinuation of LOTRONEX. Resume LOTRONEX only if their constipation has resolved and after discussion with and the agreement of their treating prescriber.immediately discontinue LOTRONEX and contact their prescriber if they become constipated, or have symptoms of ischemic colitis such as new or worsening abdominal pain, bloody diarrhea, or blood in the stool. Contact their prescriber again if their constipation does not resolve after discontinuation of LOTRONEX. Resume LOTRONEX only if their constipation has resolved and after discussion with and the agreement of their treating prescriber.
- stop taking LOTRONEX and contact their prescriber if LOTRONEX does not adequately control IBS symptoms after 4 weeks of taking 1 mg twice a day.stop taking LOTRONEX and contact their prescriber if LOTRONEX does not adequately control IBS symptoms after 4 weeks of taking 1 mg twice a day.

Medication Guide

MEDICATION GUIDE

LOTRONEX ® (LOW-trah-nex)

(alosetron hydrochloride)

Tablets

Read the Medication Guide you get with each refill for LOTRONEX. There may be new information. This Medication Guide does not take the place of talking with your doctor.

What is the most important information I should know about LOTRONEX?

LOTRONEX is a meeicine only for some women with severe chronic irritable bowel syndrome (IBS) whose:

- main problem is darrhea and
- IBS symptoms have not been helped enough by other treatments.

Some people have developed serious bowel side effects while taking LOTRONEX. Serious bowel (intestine) side effects can happen suddenly, including the following:

Serious complications of constipation:

These complications may lead to a hospital stay and, in rare cases, blood transfusions, surgery, and death. People who are older, who are weak from illness, or who take other constipating medicines may be more likely to have serious complications of constipation with LOTRONEX.

To lower your chances of getting serious complications of constipation, do the following:

- If you are constipated, do not start taking LOTRONEX.
- If you get constipated while taking LOTRONEX, stop taking it right away and call your doctor.
- If your constipation does not get better after stopping LOTRONEX, call your doctor again.
- If you stopped taking LOTRONEX, do not start taking LOTRONEX again unless your doctor tells you to do so.

- Inflammation and injury of the intestines caused by reduced blood flow (ischemic colitis): Ischemic colitis is caused by reduced blood flow to parts of the large bowel. The chance of getting ischemic colitis when you take LOTRONEX for more than 6 months is not known. Ischemic colitis may lead to a hospital stay and, in rare cases, blood transfusions, surgery, and death.

Stop taking LOTRONEX and call your doctor or get medical help if you have symptoms of ischemic colitis such as new or worsening stomach-area (abdominal) pain, bloody diarrhea or blood in the stool.

What is LOTRONEX?

LOTRONEX is a prescription medicine used only for some women wih severe chronic IBS whose:

- main problem is diarrhea and
- IBS symptoms have not been helped enough by other treatments.

LOTRONEX does not cure IBS, and it may not help every person who takes it. For those who are helped, LOTRONEX reduces lower stomach area (abdominal) pain and discomfort, the sudden need to have a bowel movement (bowel urgency), and diarrhea from IBS. If you stop taking LOTRONEX, your IBS symptoms may return within 1 or 2 weeks to what they were before you started taking LOTRONEX.

It is not known if LOTRONEX is safe and effective in men with IBS.

It is not known if LOTRONEX is safe and effective in children.

Who should not take LOTRONEX?

Do not take LOTRONEX if you:

- have constipation or you are constipated most of the time.
- have had a serious problem from constipation. If you are constipated now, do not start taking LOTRONEX.
- have had serious bowel blockages.
- have had blood flow problems to your bowels, such as ischemic colitis.
- have had blood clots.
- have had Crohn's disease, ulcerative colitis, diverticulitis, or severe liver disease.
- are taking fluvoxamine (LUVOX).

What should I talk about with my doctor before taking LOTRONEX?

Talk with your doctor:

- about the possible benefits and risks of LOTRONEX.
- about how much of a problem IBS is in your life and what treatments you have tried.
- about any other illnesses you have and medicines you take or plan to take. These include prescription and non-prescription medicines, supplements, and herbal remedies. Certain illnesses and medicines can increase your chance of getting serious side effects while taking LOTRONEX. Other medicines may interact with how the body handles LOTRONEX.
- any allergies that you have. See the end of the Medication Guide for a complete list of ingredients in LOTRONEX.
- if you have liver problems.
- if you are pregnant or planning to become pregnant. It is not known if LOTRONEX can harm your unborn baby.
- if you are breastfeeding or plan to breastfeed. It is not known if LOTRONEX can harm your baby. Talk to your doctor about the best way to feed your baby if you take LOTRONEX.

How should I take LOTRONEX?

- Take LOTRONEX exactly as your doctor prescribes it. You can take LOTRONEX with or without food.
- Begin with 0.5 mg two times a day for 4 weeks to see how LOTRONEX affects you. You and your doctor may decide that you should keep taking this dose if you are doing well.
- Check with your doctor 4 weeks after starting LOTRONEX:
- If you try 0.5 mg two times a day for 4 weeks, it may not control your symptoms. If you do not get constipation or other side

effects from LOTRONEX, your doctor may increase your dose up to 1 mg two times a day.

- If 1 mg two times a day does not work after 4 weeks, LOTRONEX is not likely to help you. You should stop taking it and call

your doctor.

- Follow the instructions in the section “What is the most important information I should know about LOTRONEX?” about when you must stop taking the medicine and when you should call your doctor.

What are the possible side effects of LOTRONEX?

LOTRONEX may cause serious side effects, including:

See "What is the most important information I should know about LOTRONEX?"

The most common side effects of LOTRONEX include:

- constipation
- stomach (abdominal) discomfort and pain
- nausea
- intestinal discomfort and pain

These are not all the possible side effects of LOTRONEX.

Call your doctor for medical advice about side effects. You may report side effects to FDA at 1-800-FDA-1088.

How should I store LOTRONEX?

- Store LOTRONEX at room temperature between 68°F to 77°F (20°C to 25°C).
- Protect LOTRONEX from light and moisture.

Keep LOTRONEX and all medicines out of the reach of children.

General information about the safe and effective use of LOTRONEX

Medicines are sometimes prescribed for purposes other than those listed in a Medication Guide. Do not use LOTRONEX for a condition for which it was not prescribed. Do not give LOTRONEX to other people, even if they have the same symptoms that you have. It may harm them. You can ask your pharmacist or healthcare provider for information about LOTRONEX that is written for healthcare professionals.

What are the ingredients of LOTRONEX?

Active Ingredient: alosetron hydrochloride

Inactive Ingredients: lactose (anhydrous), magnesium stearate, microcrystalline cellulose, and pregelatinized starch. The white film-coat for the 0.5 mg tablet contains hypromellose, titanium dioxide, and triacetin. The blue film-coat for the 1 mg tablet contains hypromellose, titanium dioxide, triacetin, and indigo carmine.

Manufactured for:
Sebela Ireland Ltd.,
Distributed By
Sebela Pharmaceuticals Inc.
645 Hembree Parkway, Suite I
Roswell, Georgia 30076

www.sebelapharma.com

Toll Free 1-844-732-3521

Made in CANADA

©2019, Sebela Pharmaceuticals Inc. All rights reserved

This product may be covered by one or more US pending or issued patents.
For details, contact www.sebelapharma.com.

LOTRONEX is a registered trademark of Sebela International Bermuda Ltd.
LUVOX is a registered trademark of Abbott Products, Inc., Abbott Park IL

This Medication Guide has been approved by the U.S. Food and Drug Administration

Revised: April 2019

PACKAGE LABEL

Principal Display Panel - Lotronex 0.5 mg Bottle Label

NDC 54766-894-03
30 Tablets
LOTRONEX
(alosetron hydrochloride) Tablets 0.5mg
Each film-coated tablet contains alosetron
hydrochloride equivalent to 0.5 mg alosetron.
Rx only
See prescribing information
For Dosage and Administration

Store at 20-25˚C (68-77˚F) (USP Controlled Room Temperature)

PACKAGE LABEL

Principal Display Panel - Lotronex 0.5 mg Carton

NDC 54766-894-03
30 Tablets
LOTRONEX
(alosetron hydrochloride)
Tablets
Rx Only 0.5 mg
Each film-coated tablet contains alosetron
hydrochloride equivalent to 0.5 mg alosetron.

Pharmacist Affix Label Here:

Federal Law requires the dispensing
of LOTRONEX ® with the Medication
Guide included in this box.

Principal Display Panel - Lotronex 1 mg Bottle Label

NDC 54766-895-03
30 Tablets
LOTRONEX
(alosetron hydrochloride) Tablets 1 mg
Each film-coated tablet contains alosetron hydrochloride
equivalent to 1 mg alosetron.
Rx only
See prescribing information
For Dosage and Administration.

Store at 20-25˚C (68-77˚F) (USP Controlled Room Temperature)

PACKAGE LABEL

Principal Display Panel - Lotronex 1 mg Carton

NDC 54766-895-03
30 Tablets
LOTRONEX
(alosetron hydrochloride)
Tablets
Rx Only 1 mg
Each film-coated tablet contains alosetron
hydrochloride equivalent to 1 mg alosetron.

Pharmacist Affix Label Here:

Federal Law requires the dispensing
of LOTRONEX ® with the Medication
Guide included in this box.